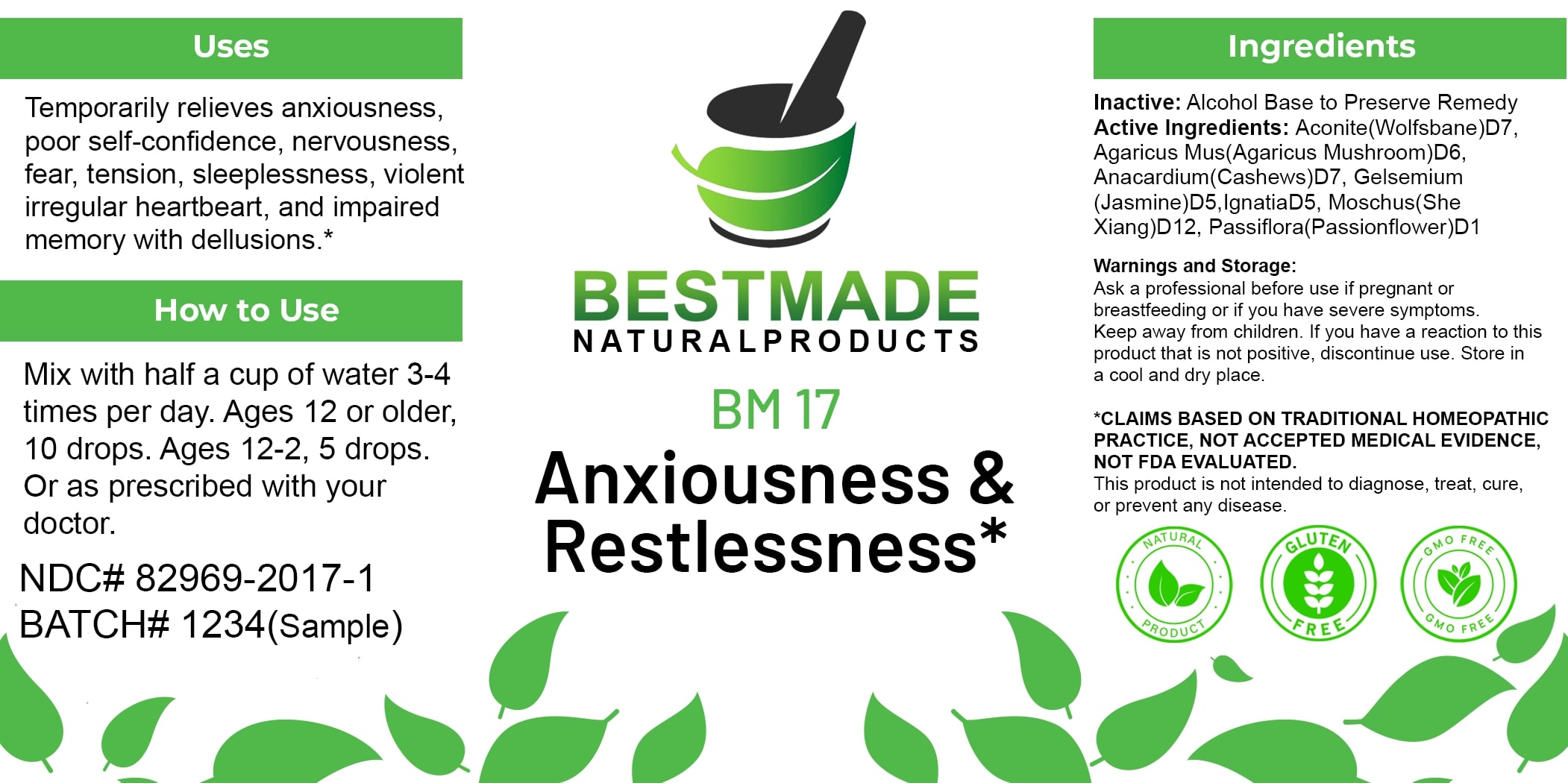 DRUG LABEL: Bestmade Natural Products BM17
NDC: 82969-2017 | Form: LIQUID
Manufacturer: Bestmade Natural Products
Category: homeopathic | Type: HUMAN OTC DRUG LABEL
Date: 20250122

ACTIVE INGREDIENTS: MOSCHUS MOSCHIFERUS MUSK SAC RESIN 30 [hp_C]/30 [hp_C]; ACONITUM NAPELLUS 30 [hp_C]/30 [hp_C]; SEMECARPUS ANACARDIUM JUICE 30 [hp_C]/30 [hp_C]; GELSEMIUM SEMPERVIRENS ROOT 30 [hp_C]/30 [hp_C]; AMANITA MUSCARIA FRUITING BODY 30 [hp_C]/30 [hp_C]; STRYCHNOS IGNATII SEED 30 [hp_C]/30 [hp_C]; PASSIFLORA INCARNATA FLOWERING TOP 30 [hp_C]/30 [hp_C]
INACTIVE INGREDIENTS: ALCOHOL 30 [hp_C]/30 [hp_C]

BM17

DOSAGE AND ADMINISTRATION

How to Use

Mix with half a cup of water 3-4 times per day. Ages 12 or older, 10 drops. Ages 12-2, 5 drops. Or as prescribed with your doctor.

INACTIVE INGREDIENT

Ingredients

Inactive: Alcohol Base to Preserve Remedy

Uses

Temporarily relieves anxiousness, poor self-confidence, nervousness, fear, tension, sleeplessness, violent irregular heartbeat, and impaired memory with delusions.*

*CLAIMS BASED ON TRADITIONAL HOMEOPATHIC PRACTICE, NOT ACCEPTED MEDICAL EVIDENCE, NOT FDA EVALUATED. This product is not intended to diagnose, treat, cure, or prevent any disease.

Active Ingredients:

Aconite(Wolfsbane)D7, Agaricus Mus(Agaricus Mushroom)D6, Anacardium(Cashews)D7, Gelsemium (Jasmine)D5, IgnatiaD5, Moschus(She Xiang)D12, Passiflora(Passionflower)D1

KEEP OUT OF REACH OF CHILDREN

Warnings and Storage:

Ask a professional before use if pregnant or breastfeeding or if you have severe symptoms. Keep away from children. If you have a reaction to this product that is not positive, discontinue use. Store in a cool and dry place.

Uses

Temporarily relieves anxiousness, poor self-confidence, nervousness, fear, tension, sleeplessness, violent irregular heartbeat, and impaired memory with delusions.*

*CLAIMS BASED ON TRADITIONAL HOMEOPATHIC PRACTICE, NOT ACCEPTED MEDICAL EVIDENCE, NOT FDA EVALUATED. This product is not intended to diagnose, treat, cure, or prevent any disease.

Warnings and Storage:

Ask a professional before use if pregnant or breastfeeding or if you have severe symptoms. Keep away from children. If you have a reaction to this product that is not positive, discontinue use. Store in a cool and dry place.

*CLAIMS BASED ON TRADITIONAL HOMEOPATHIC PRACTICE, NOT ACCEPTED MEDICAL EVIDENCE, NOT FDA EVALUATED. This product is not intended to diagnose, treat, cure, or prevent any disease.

Entire package label